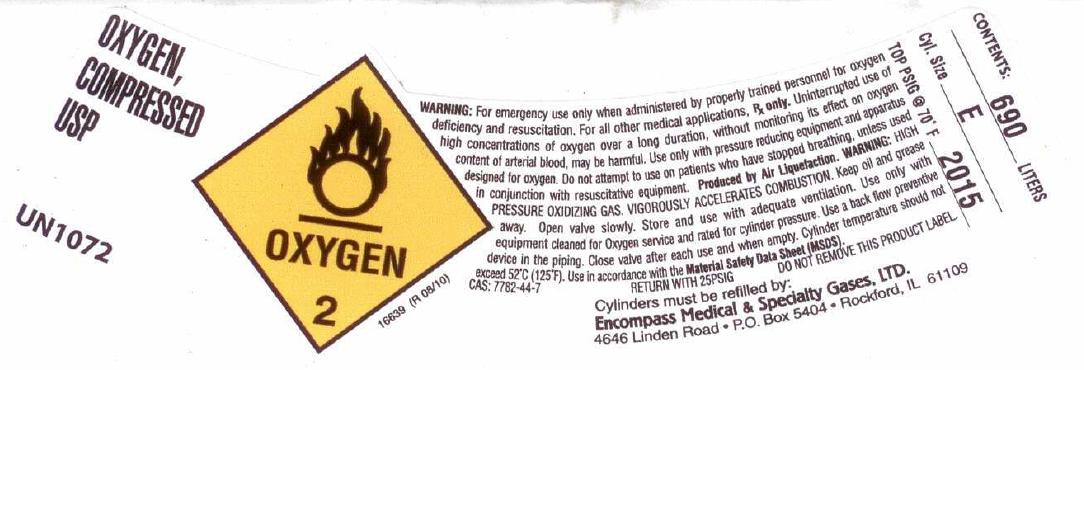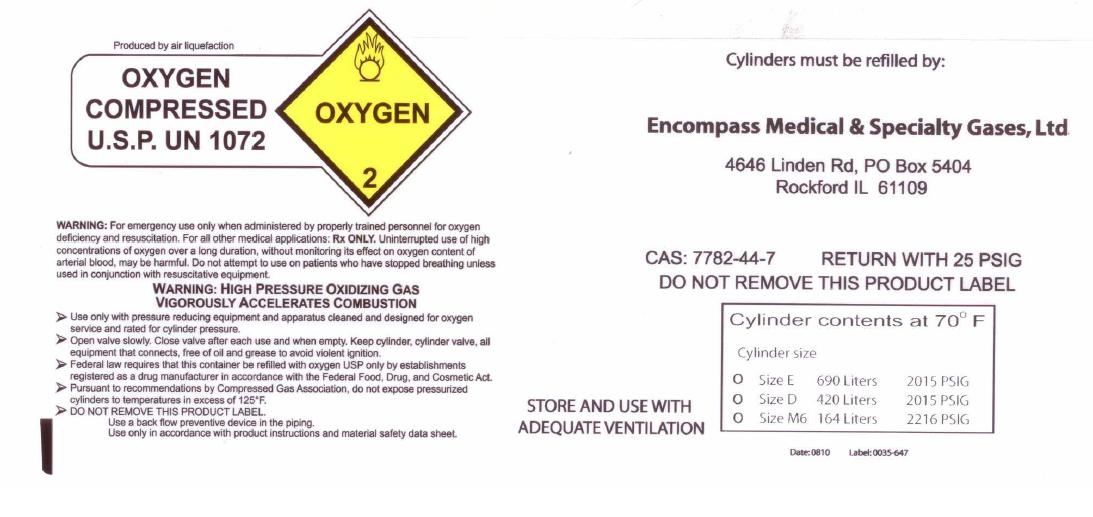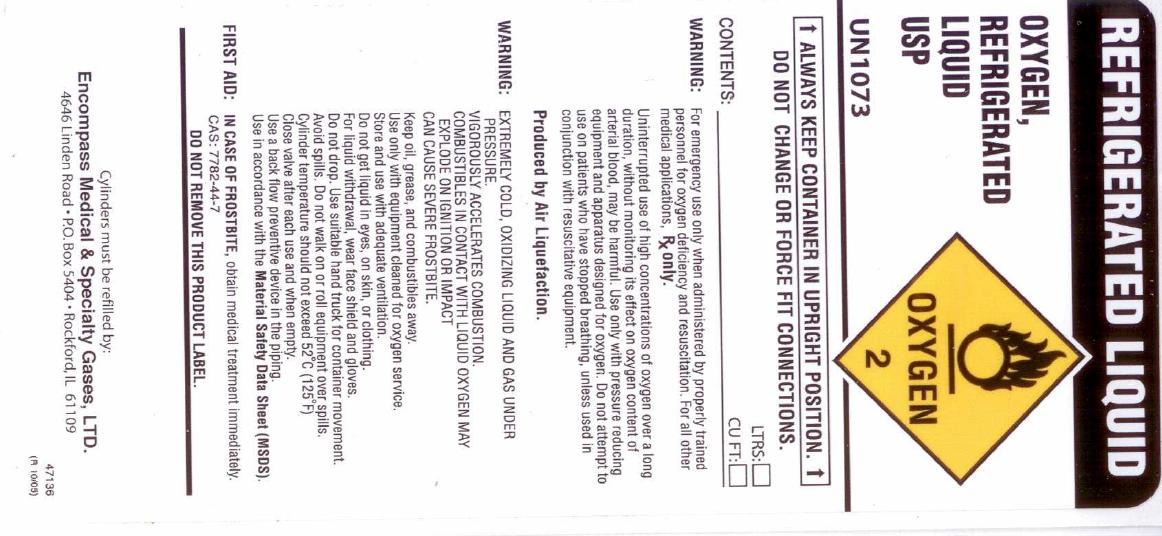 DRUG LABEL: Oxygen
NDC: 48883-001 | Form: GAS
Manufacturer: Encompass Medical & Specialty Gases, Ltd.
Category: prescription | Type: HUMAN PRESCRIPTION DRUG LABEL
Date: 20110109

ACTIVE INGREDIENTS: Oxygen 990 mL/1 L

Oxygen Label

PACKAGE LABEL

OXYGEN, Compressed USP UN1072 OXYGEN 2 16639 (R 08/10)
WARNING: For emergency use only when administered by properly trained personnel for oxygen deficiency and resuscitation. For all other medical applications, Rx ONLY. Uninterrupted use of high concentrations of oxygen over a long duration, without monitoring its effect on oxygen content of arterial blood, may be harmful. Use only with pressure reducing equipment and apparatus designed for use with oxygen. Do not attempt to use on patients who have stopped breathing unless used in conjunction with resuscitative equipment. Produced by Air Liquefaction. WARNING: HIGH PRESSURE OXIDIZING GAS. VIGOROUSLY ACCELERATES COMBUSTION. Keep oil and grease away. Open valve slowly. Store and use with adequate ventilation. Use only with equipment cleaned for Oxygen service and rated for cylinder pressure. Use a back flow preventive device in the piping. Close valve after each use and when empty. Cylinder temperature should not exceed 52 C (125F). Use in accordance with Material Safety Data Sheet (MSDS).
CAS: 7782-44-7 RETURN WITH 25 PSIG
DO NOT REMOVE THIS PRODUCT LABEL.
Cylinders must be refilled by:
Encompass Medical and Specialty Gases, LTD. 4646 Linden Road P.O. Box 5404 Rockford, IL 61109
CONTENTS: 690 LTRS CYL. SIZE E TOP PSIG at 70 F 2015

PACKAGE LABEL

REFRIGERATED LIQUID
OXYGEN, REFRIGERATED LIQUID USP UN1073 OXYGEN 2
ALWAYS KEEP CONTAINER IN UPRIGHT POSITION. DO NOT CHANGE OR FORCE FIT CONNECTIONS.
CONTENTS: LTRS. CU. FT.
WARNING: For emergency use only when administered by properly trained personnel for oxygen deficiency and resuscitation. For all other medical applications, Rx ONLY. Uninterrupted use of high concentrations of oxygen over a long duration, without monitoring its effect on oxygen content of arterial blood, may be harmful. Use only with pressure reducing equipment and apparatus designed for use with oxygen. Do not attempt to use on patients who have stopped breathing unless used in conjunction with resuscitative equipment. Produced by Air Liquefaction.
WARNING: EXTREMELY COLD, OXIDIZING LIQUID AND GAS UNDER PRESSURE . VIGOROUSLY ACCELERATES COMBUSTION. COMBUSTIBLES IN CONTACT WITH LIQUID OXYGEN MAY EXPLODE ON IGNITION OR IMPACT. CAN CAUSE SEVERE FROSTBITE.
Keep oil, grease and combustibles away. Use only with equipment cleaned for oxygen. Store and use with adequate ventilation. Do not get liquid in eyes, on skin, or clothing. For liquid withdrawal, wear face shield and gloves. Do not drop. Use suitable hand truck for container movement. Avoid spills. O not walk on or roll equipment over spills. Cylinder temperature should not exceed 52 C (125F). Close valve after each use and when empty. Use a back flow preventive device in the piping. Use in accordance with Material Safety Data Sheet (MSDS). FIRST AID : IN CASE OF FROSTBITE, obtain medical treatment immediately.
CAS: 7782-44-7
DO NOT REMOVE THIS PRODUCT LABEL.
Cylinders must be refilled by:
Encompass Medical and Specialty Gases, LTD. 4646 Linden Road P.O. Box 5404 Rockford, IL 61109
47136 (R 10/05)

PACKAGE LABEL

Produced by air liquefaction
OXYGEN, Compressed U.S.P. UN1072 OXYGEN 2
WARNING: For emergency use only when administered by properly trained personnel for oxygen deficiency and resuscitation. For all other medical applications, Rx ONLY. Uninterrupted use of high concentrations of oxygen over a long duration, without monitoring its effect on oxygen content of arterial blood, may be harmful. Do not attempt to use on patients who have stopped breathing unless used in conjunction with resuscitative equipment.
WARNING: HIGH PRESSURE OXIDIZING GAS. VIGOROUSLY ACCELERATES COMBUSTION.
Use only with pressure reducing equipment and apparatus cleaned and designed for oxygen service and rated for cylinder pressure. Open valve slowly. Close valve after each use and when empty. Keep cylinder, cylinder valve, all equipment that connects, free of oil and grease to avoid violent ignition. Federal law requires that this container be refilled with oxygen USP only by establishments registered as a drug manufacturer in accordance with the Federal Food, Drug and Cosmetic Act. Pursuant to recommendations by the Compressed Gas Association, do not expose pressurized cylinders to temperatures in excess of 125F. DO NOT REMOVE THIS PRODUCT LABEL.
Use a back flow preventive device in the piping. Use only in accordance with product instructions and Material Safety Data Sheet.
Cylinders must be refilled by:
Encompass Medical and Specialty Gases, LTD. 4646 Linden Road P.O. Box 5404 Rockford, IL 61109
CAS: 7782-44-7 RETURN WITH 25 PSIG
DO NOT REMOVE THIS PRODUCT LABEL
Cylinder contents at 70F
Cylinder size
Size E 690 liters 2015 PSIG
Size D 420 Liters 2015 PSIG
Size M6 164 Liters 2015 PSIG
STORE AND USE WITH ADEQUATE VENTILATION
Date: 0810 Label:0035-647